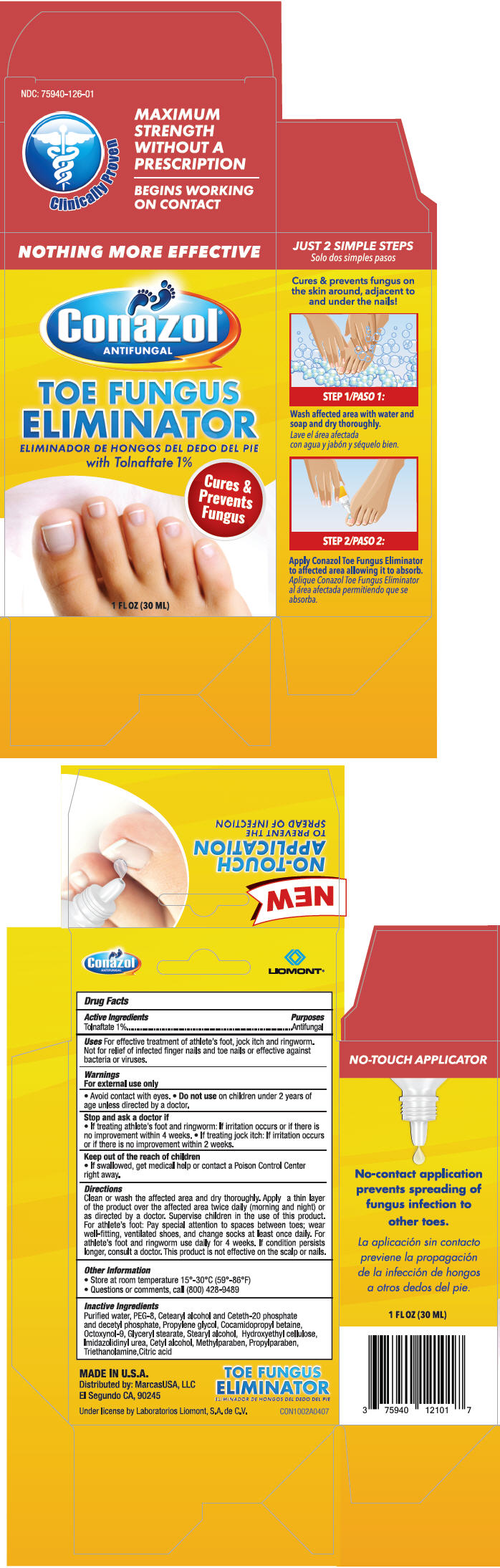 DRUG LABEL: Conazol
NDC: 75940-126 | Form: SOLUTION/ DROPS
Manufacturer: MarcusUSA
Category: otc | Type: HUMAN OTC DRUG LABEL
Date: 20200127

ACTIVE INGREDIENTS: Tolnaftate 10 mg/1 mL
INACTIVE INGREDIENTS: water; POLYETHYLENE GLYCOL 400; CETOSTEARYL ALCOHOL; CETETH-20 PHOSPHATE; DIETHANOLAMINE CETYL PHOSPHATE; propylene glycol; cocamidopropyl betaine; octoxynol-9; GLYCERYL MONOSTEARATE; Stearyl alcohol; HYDROXYETHYL CELLULOSE (3000 MPA.S AT 1%); IMIDUREA; CETYL ALCOHOL; methylparaben; PROPYLPARABEN; TROLAMINE; CITRIC ACID MONOHYDRATE

Conazol®
antifungal

Drug Facts

Active Ingredients

Tolnaftate 1%

Purposes

Antifungal

Uses

For effective treatment of athlete's foot, jock itch and ringworm. Not for relief of infected finger nails and toe nails or effective against bacteria or viruses.

Warnings

For external use only

DO NOT USE

- Avoid contact with eyes.
- Do not use on children under 2 years of age unless directed by a doctor.

Stop and ask a doctor if

- If treating athlete's foot and ringworm: If irritation occurs or if there is no improvement within 4 weeks.
- If treating jock itch: If irritation occurs or if there is no improvement within 2 weeks.

Keep out of the reach of children

- If swallowed, get medical help or contact a Poison Control Center right away.

Directions

Clean or wash the affected area and dry thoroughly. Apply a thin layer of the product over the affected area twice daily (morning and night) or as directed by a doctor. Supervise children in the use of this product. For athlete's foot: Pay special attention to spaces between toes; wear well-fitting, ventilated shoes, and change socks at least once daily. For athlete's foot and ringworm use daily for 4 weeks. If condition persists longer, consult a doctor. This product is not effective on the scalp or nails.

Other Information

- Store at room temperature 15°-30°C (59°-86°F)

- Questions or comments, call (800) 428-9489

Inactive Ingredients

Purified water, PEG-8, Cetearyl alcohol and Ceteth-20 phosphate and decetyl phosphate, Propylene glycol, Cocamidopropyl betaine, Octoxynol-9, Glyceryl stearate, Stearyl alcohol, Hydroxyethyl cellulose, Imidazolidinyl urea, Cetyl alcohol, Methylparaben, Propylparaben, Triethanolamine,Citric acid

Distributed by: MarcasUSA, LLC
El Segundo CA, 90245

PRINCIPAL DISPLAY PANEL - 30 ML Bottle Carton

NOTHING MORE EFFECTIVE

Conazol®
ANTIFUNGAL

TOE FUNGUS
ELIMINATOR
with Tolnaftate 1%

Cures &
Prevents
Fungus

1 FL OZ (30 ML)